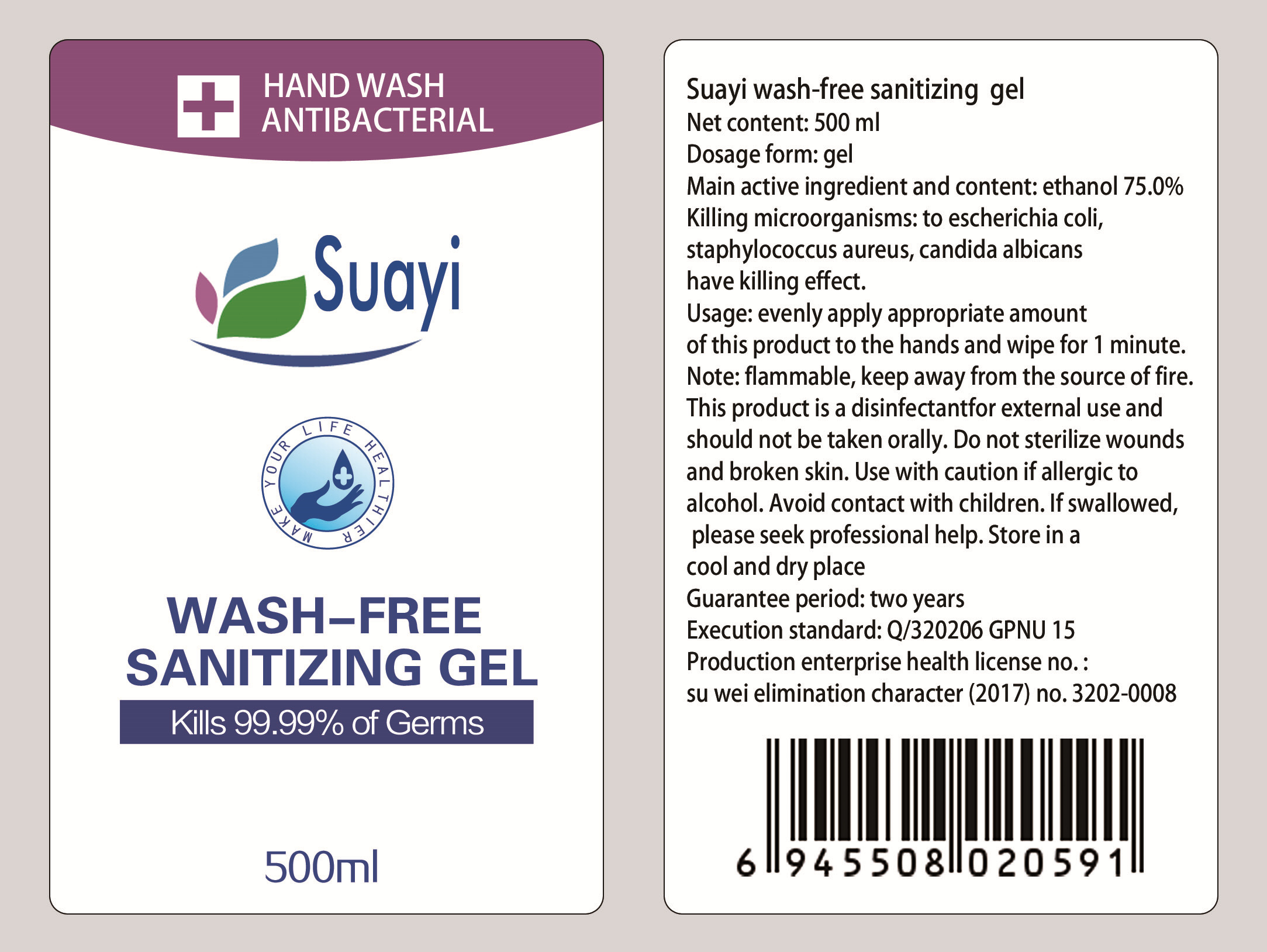 DRUG LABEL: HAND WASH ANTIBACTERIAL
NDC: 54607-002 | Form: GEL
Manufacturer: Wuxi Yongning Daily Chemical Factory
Category: otc | Type: HUMAN OTC DRUG LABEL
Date: 20200329

ACTIVE INGREDIENTS: ALCOHOL 375 mL/500 mL
INACTIVE INGREDIENTS: WATER; GLYCERIN; CARBOMER HOMOPOLYMER, UNSPECIFIED TYPE; TROLAMINE

WARNINGS

This product is a disinfectantfor external use and should not be taken orally.

Do not sterilize woundsand broken skin.

INACTIVE INGREDIENT

Carbomer glycerol Triethanolamine

PURPOSE

Disinfection
Sterilization
No Rinseing

ACTIVE INGREDIENT

ethanol

keep out of reach of children

DOSAGE AND ADMINISTRATION

Flammable, keep away from the source of fire.

INDICATIONS AND USAGE

Evenly apply appropriate amount of this product to the hands and wipe for 1 minute.